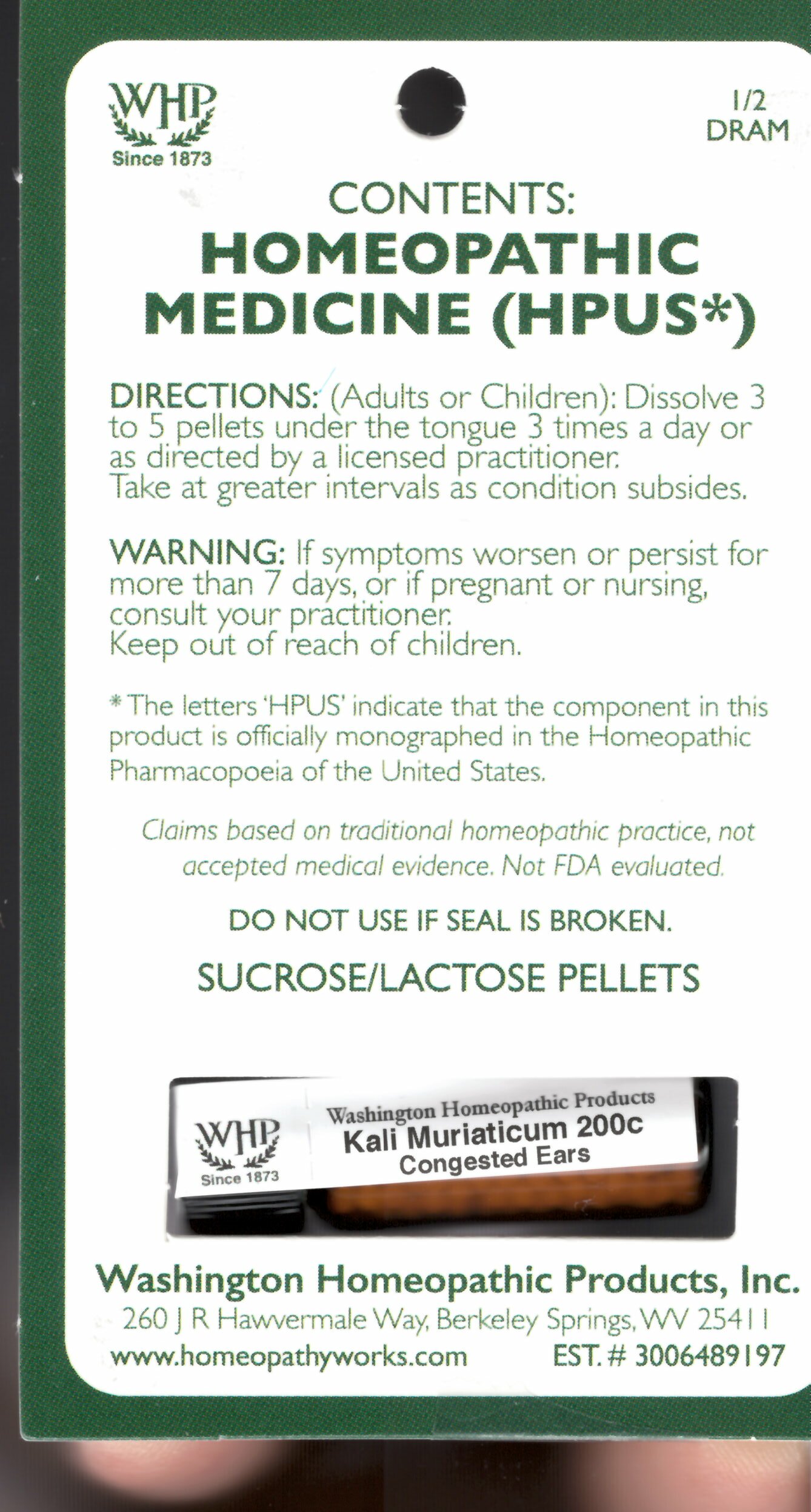 DRUG LABEL: Kali Muriaticum Kit Refill
NDC: 71919-813 | Form: PELLET
Manufacturer: Washington Homeopathic Products
Category: homeopathic | Type: HUMAN OTC DRUG LABEL
Date: 20250128

ACTIVE INGREDIENTS: POTASSIUM CHLORIDE 200 [hp_C]/1 1
INACTIVE INGREDIENTS: SUCROSE; LACTOSE

Kali muriaticum Kit Refill 200c

ACTIVE INGREDIENTS

KALI MURIATICUM 30C

USES

To relieve the symptoms of congested ears.

KEEP OUT OF REACH OF CHILDREN

Keep this and all medicines out of reach of children.

INDICATIONS

KALI MURIATICUM Congested ears

STOP USE AND ASK DOCTOR

If symptoms persist/worsen or if pregnant/nursing, stop use and consult your practitioner.

DIRECTIONS

Adults: Dissolve 3 to 5 under the tongue three times a day or as directed by Lic. Practitioner. Take at greater intervals as condition subsides.

Children: Dissolve 3 to 5 under the tongue three times a day or as directed by Lic. Practitioner. Take at greater intervals as condition subsides.

INACTIVE INGREDIENTS

Sucrose/Lactose